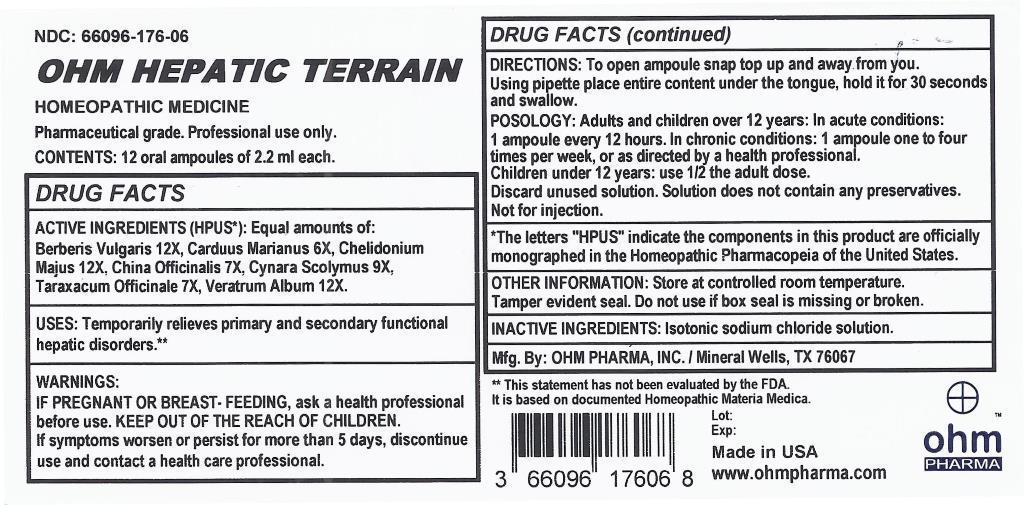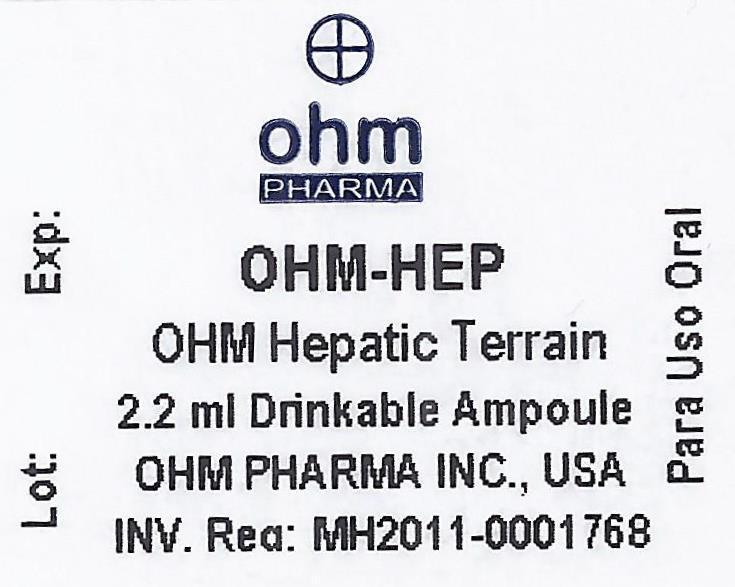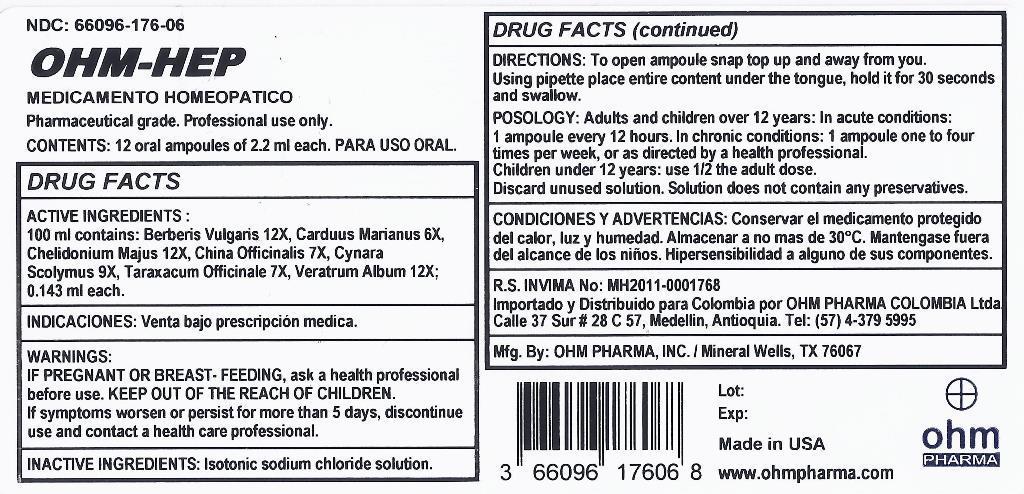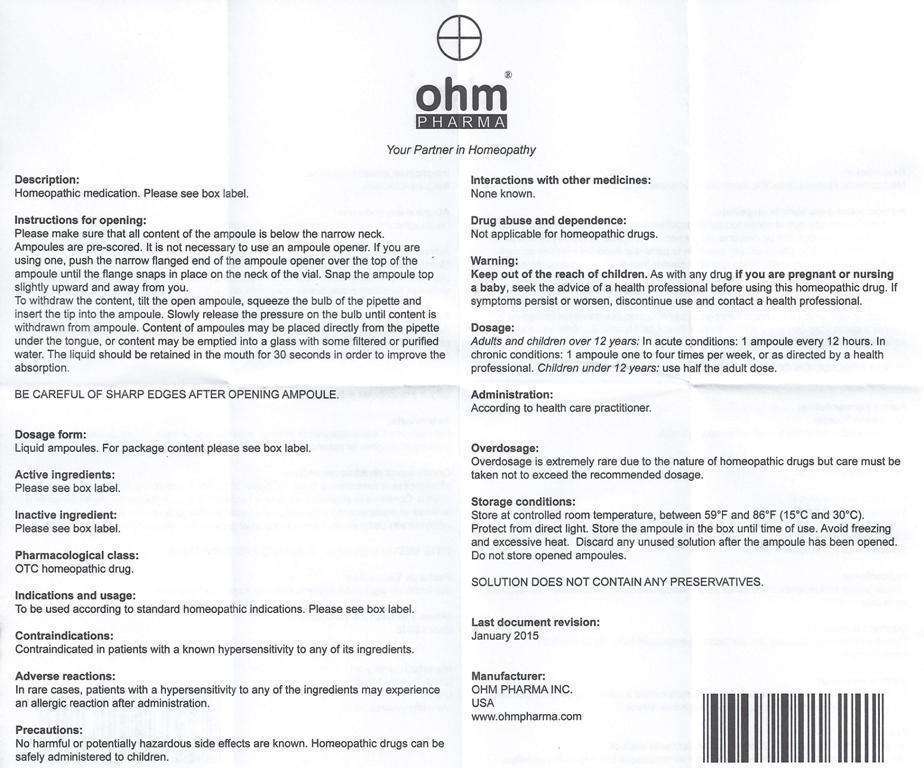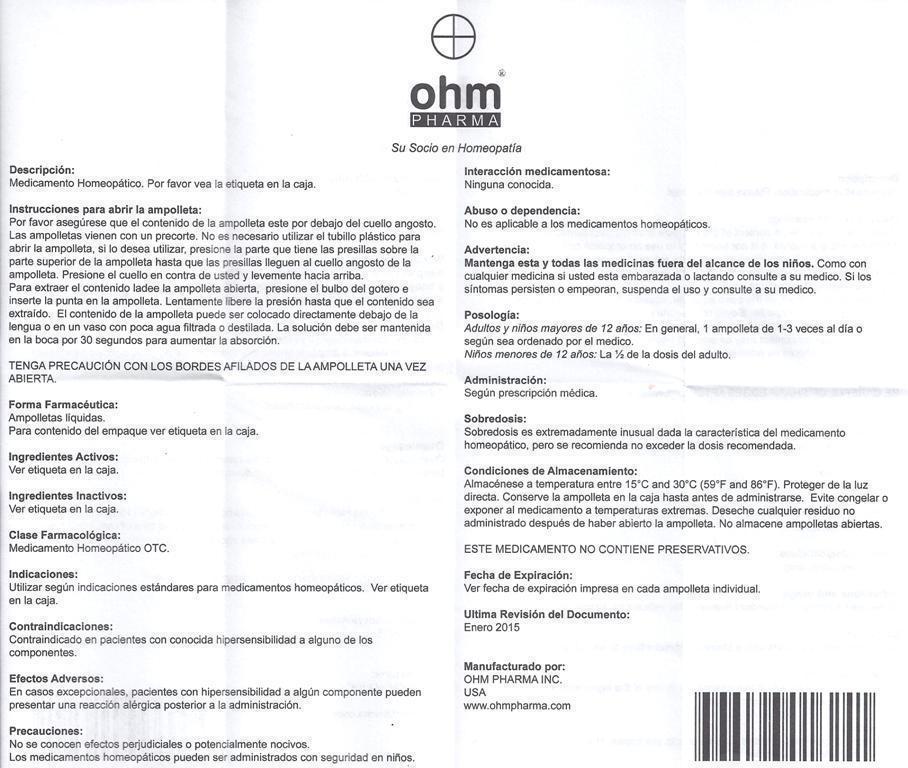 DRUG LABEL: OHM HEPATIC TERRAIN
NDC: 66096-176 | Form: LIQUID
Manufacturer: OHM PHARMA INC.
Category: homeopathic | Type: HUMAN OTC DRUG LABEL
Date: 20210111

ACTIVE INGREDIENTS: BERBERIS VULGARIS ROOT BARK 12 [hp_X]/1 mL; MILK THISTLE 6 [hp_X]/1 mL; CHELIDONIUM MAJUS 12 [hp_X]/1 mL; CINCHONA OFFICINALIS BARK 7 [hp_X]/1 mL; CYNARA SCOLYMUS LEAF 9 [hp_X]/1 mL; TARAXACUM OFFICINALE 7 [hp_X]/1 mL; VERATRUM ALBUM ROOT 12 [hp_X]/1 mL
INACTIVE INGREDIENTS: SODIUM CHLORIDE

OHM HEPATIC TERRAIN

ACTIVE INGREDIENT

ACTIVE INGREDIENTS (HPUS*): Equal amounts of: Berberis Vulgaris 12X, Carduus Marianus 6X, Chelidonium Majus 12X, China Officinalis 7X, Cynara Scolymus 9X, Taraxacum Officinale 7X, Veratrum Album 12X.

ACTIVE INGREDIENT

*The letters "HPUS" indicate the components in this product are officially monographed in the Homeopathic Pharmacopeia of the United States.

INDICATIONS AND USAGE

USES: Temporarily relieves primary and secondary functional hepatic disorders.**

**This statement has not been evaluated by the FDA.
It is based on documented Homeopathic Materia Medica.

WARNINGS:

IF PREGNANT OR BREAST-FEEDING, ask a health professional before use. If symptoms worsen or persist for more than 5 days, discontinue use and contact a health care professional.

KEEP OUT OF THE REACH OF CHILDREN.

DOSAGE AND ADMINISTRATION

DIRECTIONS: To open ampoule snap top up and away from you. Using pipette place entire content under the tongue, hold it for 30 seconds and swallow.

POSOLOGY: Adults and children over 12 years: In acute conditions: 1 ampoule every 12 hours. In chronic conditions: 1 ampoule one to four times per week, or as directed by a health professional.

Children under 12 years use 1/2 the adult dose.

Discard unused solution. Solution does not contain any preservatives.

Not for injection.

OTHER INFORMATION: Store at controlled room temperature. Tamper evident seal. Do not use if box seal is missing or broken.

INACTIVE INGREDIENTS: Isotonic sodium chloride solution.

QUESTIONS

Mfg. By: OHM PHARMA, INC. / Mineral Wells, TX 76067

Made in USA

www.ohmpharma.com

PURPOSE

Primary and secondary functional hepatic disorders relief

PACKAGE LABEL

NDC: 66096-176-06

OHM HEPATIC TERRAIN

HOMEOPATHIC MEDICINE

Pharmaceutical Grade. Professional use only.

CONTENTS: 12 oral ampoules of 2.2 ml each.